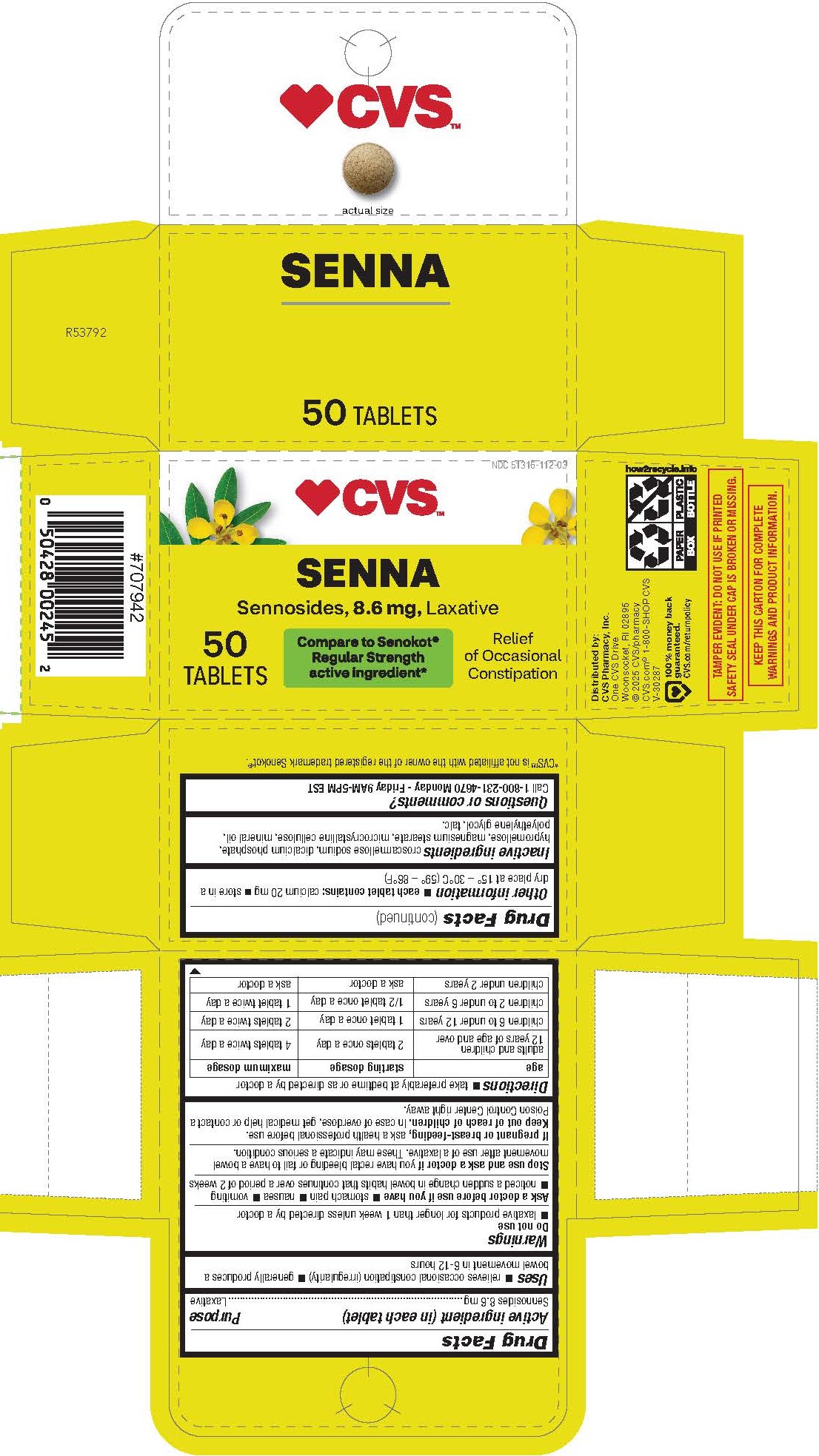 DRUG LABEL: Sennosides
NDC: 51316-112 | Form: TABLET, FILM COATED
Manufacturer: CVS Pharmacy, Inc
Category: otc | Type: HUMAN OTC DRUG LABEL
Date: 20260226

ACTIVE INGREDIENTS: SENNOSIDES 8.6 mg/1 1
INACTIVE INGREDIENTS: LIGHT MINERAL OIL; HYPROMELLOSES; MAGNESIUM STEARATE; CALCIUM PHOSPHATE, DIBASIC, DIHYDRATE; TALC; MICROCRYSTALLINE CELLULOSE; CROSCARMELLOSE SODIUM; POLYETHYLENE GLYCOL 400

1122W-CVS

Drug Facts

Active ingredient (in each tablet)
Sennosides 8.6 mg

Purpose
Laxative

Uses

 relieves occasional constipation (irregularity)

 generally produces a bowel movement in 6-12 hours

WARNINGS

DO NOT USE

 laxative products for longer than 1 week unless directed by a doctor

Ask a doctor before use if you have

 stomach pain

 nausea

 vomiting
 noticed a sudden change in bowel habits that continues over a period of 2 weeks

Stop use and ask a doctor if you have rectal bleeding or fail to have a bowel movement after use of a laxative. These may indicate a serious condition.

PREGNANCY OR BREAST FEEDING

If pregnant or breast-feeding, ask a health professional before use.

Keep out of reach of children.

OVERDOSAGE

In case of overdose, get medical help or contact a Poison Control Center right away.

Directions

 take preferably at bedtime or as directed by a doctor

Age | starting dosage | maximum dosage
adults and children 12 years of age and over | 2 tablets once a day | 4 tablets twice a day
children 6 to under 12 years | 1 tablet once a day | 2 tablets twice a day
children 2 to under 6 years | 1/2 tablet once a day | 1 tablet twice a day
children under 2 years | ask a doctor | ask a doctor

Other information

 each tablet contains: calcium 20 mg

 store in a dry place at 15° – 30°C (59° – 86°F)

INACTIVE INGREDIENT

croscarmellose sodium, dicalcium phosphate, hypromellose, magnesium stearate, microcrystalline cellulose, mineral oil, polyethylene glycol, talc.

QUESTIONS

Call 1-800-231-4670 Monday - Friday 9AM-5PM EST

Distributed by:

CVS Pharmacy, Inc.
One CVS Drive
Woonsocket, RI 02895
© 2025 CVS/pharmacy
CVS.com® 1-800-SHOP CVS

TAMPER EVIDENT: DO NOT USE IF PRINTED SAFETY SEAL UNDER CAP IS BROKEN OR MISSING.

KEEP THIS CARTON FOR COMPLETE WARNINGS AND PRODUCT INFORMATION.

*CVS™ is not affiliated with the owner of the registered trademark Senokot®.

PACKAGE LABEL

CVS™

NDC 51316-112-03

SENNA

Sennosides, 8.6 mg, Laxative

Compare to Senokot® Regular Strength active ingredient*

Relief of Occasional Constipation

50 TABLETS